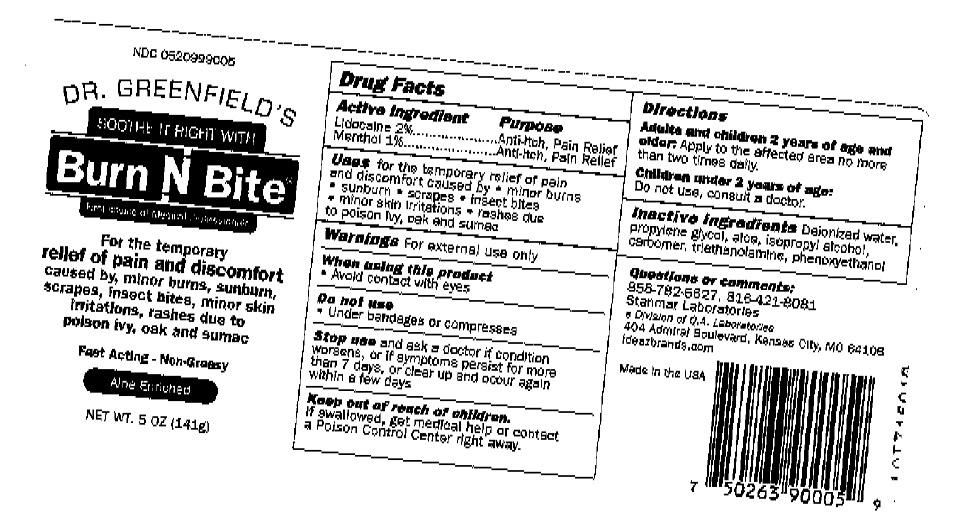 DRUG LABEL: BURN N BITE
NDC: 52099-9005 | Form: GEL
Manufacturer: Q.A. Laboratories
Category: otc | Type: HUMAN OTC DRUG LABEL
Date: 20220117

ACTIVE INGREDIENTS: LIDOCAINE 2 g/100 g; MENTHOL, UNSPECIFIED FORM 1 g/100 g
INACTIVE INGREDIENTS: WATER; PROPYLENE GLYCOL; ALOE; ISOPROPYL ALCOHOL; CARBOMER HOMOPOLYMER, UNSPECIFIED TYPE; TROLAMINE; PHENOXYETHANOL

Burn N Bite

Active Ingredient

Lidocaine 2%
Menthol 1%

Purpose

Ant-itch, Pain Relief

Uses

for the temporary relief of pain and discomfort caused by • minor burns • sunburn • scrapes • insect bites • minor skin irritations • rashes due to poison ivy, oak and sumac.

Warnings

For external use only.

When using this product

• Avoid contact with eyes

Do not use

• Under bandages or compresses

Stop use and ask a doctor if condition worsens, or if symptoms persist for more than 7 days or clear up and occur again within a few days

Keep out of reach of children.

If swallowed, get medical help or contact a Poison Control Center right away.

Directions

Adults and children 2 years of age and older: Apply to the affected area not more than two times daily.

Children under 2 years of age: Do not use, consult a doctor

Inactive Ingredients

Deionized water, propylene glycol, aloe, isopropyl alcohol, carbomer, triethanolamine, phenoxyethanol

Questions or comments:

858-782-6627, 816-421-8081

Stanmar Laboratories

Division of Q.A. Laboratories

404 Admiral Boulevard Kansas City, MO 64106

Ideazbrands.com

Made in the USA